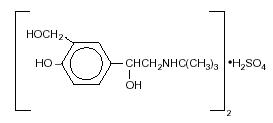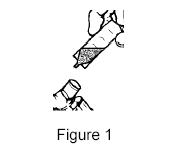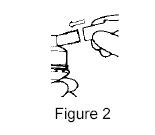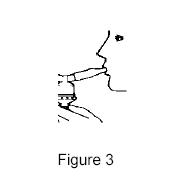 DRUG LABEL: Unknown
Manufacturer: Holopack International
Category: prescription | Type: HUMAN PRESCRIPTION DRUG LABEL
Date: 20081231

Albuterol Sulfate Inhalation Solution, 0.083%*
*Potency expressed as albuterol.
Rx Only
FOR ORAL INHALATION ONLY

DESCRIPTION

Albuterol Sulfate Inhalation Solution is a relatively selective beta2-adrenergic bronchodilator (see CLINICAL PHARMACOLOGY). Albuterol sulfate, USP, the racemic form of albuterol, has the chemical name α^1-[(tert-Butylamino)methyl]-4-hydroxy-m-xylene-α,α'-diol sulfate (2:1) (salt) and the following structural formula:

Albuterol sulfate has a molecular weight of 576.71, and the molecular formula is (C13H21NO3)2 • H2SO4. Albuterol sulfate is a white crystalline powder, soluble in water and slightly soluble in ethanol.

The World Health Organization recommended name for albuterol base is salbutamol.

Albuterol Sulfate Inhalation Solution requires no dilution before administration by nebulization.

Each milliliter of Albuterol Sulfate Inhalation Solution contains 0.83 mg of albuterol (as 1 mg of albuterol sulfate) in an isotonic, sterile, aqueous solution containing sodium chloride; sulfuric acid is used to adjust the pH to between 3 and 5. Albuterol Sulfate Inhalation Solution contains no sulfiting agents or preservatives.

Albuterol Sulfate Inhalation Solution is a clear, colorless to light yellow solution.

CLINICAL PHARMACOLOGY

In vitro studies and in vivo pharmacologic studies have demonstrated that albuterol has a preferential effect on beta2-adrenergic receptors compared with isoproterenol. While it is recognized that beta2-adrenergic receptors are the predominant receptors in bronchial smooth muscle, data indicate that 10% to 50% of the beta-receptors in the human heart may be beta2-receptors. The precise function of these receptors has not been established.

The pharmacologic effects of beta-adrenergic agonist drugs, including albuterol, are at least in part attributable to stimulation through beta-adrenergic receptors of intracellular adenyl cyclase, the enzyme that catalyzes the conversion of adenosine triphosphate (ATP) to cyclic-3',5'-adenosine monophosphate (cyclic AMP). Increased cyclic AMP levels are associated with relaxation of bronchial smooth muscle and inhibition of release of mediators of immediate hypersensitivity from cells, especially from mast cells.

Albuterol has been shown in most controlled clinical trials to have more effect on the respiratory tract, in the form of bronchial smooth muscle relaxation, than isoproterenol at comparable doses while producing fewer cardiovascular effects.

Controlled clinical studies and other clinical experience have shown that inhaled albuterol, like other beta-adrenergic agonist drugs, can produce a significant cardiovascular effect in some patients, as measured by pulse rate, blood pressure, symptoms, and/or electrocardiographic changes.

Albuterol is longer acting than isoproterenol in most patients by any route of administration because it is not a substrate for the cellular uptake processes for catecholamines nor for catechol-O-methyl transferase.

Pharmacokinetics

Studies in asthmatic patients have shown that less than 20% of a single albuterol dose was absorbed following either IPPB (intermittent positive-pressure breathing) or nebulizer administration; the remaining amount was recovered from the nebulizer and apparatus and expired air. Most of the absorbed dose was recovered in the urine 24 hours after drug administration. Following a 3-mg dose of nebulized albuterol in adults, the maximum albuterol plasma levels at 0.5 hours were 2.1 ng/mL (range, 1.4 to 3.2 ng/mL). There was a significant dose-related response in FEV1 (forced expiratory volume in one second) and peak flow rate. It has been demonstrated that following oral administration of 4 mg of albuterol, the elimination half-life was 5 to 6 hours.

Preclinical

Intravenous studies in rats with albuterol sulfate have demonstrated that albuterol crosses the blood-brain barrier and reaches brain concentrations amounting to approximately 5.0% of the plasma concentrations. In structures outside the blood-brain barrier (pineal and pituitary glands), albuterol concentrations were found to be 100 times those in the whole brain.

Studies in laboratory animals (minipigs, rodents, and dogs) have demonstrated the occurrence of cardiac arrhythmias and sudden death (with histologic evidence of myocardial necrosis) when beta-agonists and methylxanthines were administered concurrently. The clinical significance of these findings is unknown.

Clinical Trials

In controlled clinical trials in adults, most patients exhibited an onset of improvement in pulmonary function within 5 minutes as determined by FEV1. FEV1 measurements also showed that the maximum average improvement in pulmonary function usually occurred at approximately 1 hour following inhalation of 2.5 mg of albuterol by compressor-nebulizer and remained close to peak for 2 hours. Clinically significant improvement in pulmonary function (defined as maintenance of a 15% or more increase in FEV1 over baseline values) continued for 3 to 4 hours in most patients, with some patients continuing up to 6 hours.

Published reports of trials in asthmatic children aged 3 years or older have demonstrated significant improvement in either FEV1 or PEFR within 2 to 20 minutes following single doses of albuterol inhalation solution. An increase of 15% or more in baseline FEV1 has been observed in children aged 5 to 11 years up to 6 hours after treatment with doses of 0.10 mg/kg or higher of albuterol inhalation solution. Single doses of 3, 4, or 10 mg resulted in improvement in baseline PEFR that was comparable in extent and duration to a 2-mg dose, but doses above 3 mg were associated with heart rate increases of more than 10%.

INDICATIONS AND USAGE

Albuterol Sulfate Inhalation Solution is indicated for the relief of bronchospasm in patients 2 years of age and older with reversible obstructive airway disease and acute attacks of bronchospasm.

CONTRAINDICATIONS

Albuterol Sulfate Inhalation Solution is contraindicated in patients with a history of hypersensitivity to albuterol or any of its components.

WARNINGS

Paradoxical Bronchospasm

Albuterol Sulfate Inhalation Solution can produce paradoxical bronchospasm, which may be life threatening. If paradoxical bronchospasm occurs, Albuterol Sulfate Inhalation Solution should be discontinued immediately and alternative therapy instituted. It should be recognized that paradoxical bronchospasm, when associated with inhaled formulations, frequently occurs with the first use of a new canister or vial.

Cardiovascular Effects

Albuterol Sulfate Inhalation Solution, like all other beta-adrenergic agonists, can produce a clinically significant cardiovascular effect in some patients as measured by pulse rate, blood pressure, and/or symptoms. Although such effects are uncommon after administration of Albuterol Sulfate Inhalation Solution at recommended doses, if they occur, the drug may need to be discontinued. In addition, beta-agonists have been reported to produce electrocardiogram (ECG) changes, such as flattening of the T wave, prolongation of the QTc interval, and ST segment depression. The clinical significance of these findings is unknown. Therefore, Albuterol Sulfate Inhalation Solution, like all sympathomimetic amines, should be used with caution in patients with cardiovascular disorders, especially coronary insufficiency, cardiac arrhythmias, and hypertension.

Deterioration of Asthma

Asthma may deteriorate acutely over a period of hours or chronically over several days or longer. If the patient needs more doses of Albuterol Sulfate Inhalation Solution than usual, this may be a marker of destabilization of asthma and requires reevaluation of the patient and treatment regimen, giving special consideration to the possible need for anti-inflammatory treatment, e.g., corticosteroids.

Immediate hypersensitivity reactions may occur after administration of albuterol, as demonstrated by rare cases of urticaria, angioedema, rash, bronchospasm, and oropharyngeal edema.

Use of Anti-Inflammatory Agents

The use of beta-adrenergic agonist bronchodilators alone may not be adequate to control asthma in many patients. Early consideration should be given to adding anti-inflammatory agents, e.g., corticosteroids.

PRECAUTIONS

General

Albuterol, as with all sympathomimetic amines, should be used with caution in patients with cardiovascular disorders, especially coronary insufficiency, cardiac arrhythmias, and hypertension; in patients with convulsive disorders, hyperthyroidism, or diabetes mellitus; and in patients who are unusually responsive to sympathomimetic amines. Clinically significant changes in systolic and diastolic blood pressure have been seen in individual patients and could be expected to occur in some patients after use of any beta-adrenergic bronchodilator.

Large doses of intravenous albuterol have been reported to aggravate pre-existing diabetes mellitus and ketoacidosis. As with other beta-agonists, albuterol may produce significant hypokalemia in some patients, possibly through intracellular shunting, which has the potential to produce adverse cardiovascular effects. The decrease is usually transient, not requiring supplementation.

Repeated dosing with 0.15 mg/kg of albuterol inhalation solution in children aged 5 to 17 years who were initially normokalemic has been associated with an asymptomatic decline of 20% to 25% in serum potassium levels.

Information For Patients

The action of Albuterol Sulfate Inhalation Solution may last up to 6 hours or longer. Albuterol Sulfate Inhalation Solution should not be used more frequently than recommended. Do not increase the dose or frequency of Albuterol Sulfate Inhalation Solution without consulting your physician. If you find that treatment with Albuterol Sulfate Inhalation Solution becomes less effective for symptomatic relief, your symptoms become worse, and/or you need to use the product more frequently than usual, you should seek medical attention immediately. While you are using Albuterol Sulfate Inhalation Solution, other inhaled drugs and asthma medications should be taken only as directed by your physician. Common adverse effects include palpitations, chest pain, rapid heart rate, and tremor or nervousness. If you are pregnant or nursing, contact your physician about use of Albuterol Sulfate Inhalation Solution. Effective and safe use of Albuterol Sulfate Inhalation Solution includes an understanding of the way that it should be administered.

Drug compatibility (physical and chemical), efficacy, and safety of Albuterol Sulfate Inhalation Solution when mixed with other drugs in a nebulizer have not been established.

See illustrated Patient's Instructions for Use.

Drug Interactions

Other short-acting sympathomimetic aerosol bronchodilators or epinephrine should not be used concomitantly with albuterol. If additional adrenergic drugs are to be administered by any route, they should be used with caution to avoid deleterious cardiovascular effects.

Monoamine Oxidase Inhibitors or Tricyclic Antidepressants

Albuterol should be administered with extreme caution to patients being treated with monoamine oxidase inhibitors or tricyclic antidepressants, or within 2 weeks of discontinuation of such agents, because the action of albuterol on the vascular system may be potentiated.

Beta-Blockers

Beta-adrenergic receptor blocking agents not only block the pulmonary effect of beta-agonists, such as Albuterol Sulfate Inhalation Solution, but may produce severe bronchospasm in asthmatic patients. Therefore, patients with asthma should not normally be treated with betablockers. However, under certain circumstances, e.g., as prophylaxis after myocardial infarction, there may be no acceptable alternatives to the use of beta-adrenergic blocking agents in patients with asthma. In this setting, cardioselective beta-blockers could be considered, although they should be administered with caution.

Diuretics

The ECG changes and/or hypokalemia that may result from the administration of nonpotassium-sparing diuretics (such as loop or thiazide diuretics) can be acutely worsened by beta-agonists, especially when the recommended dose of the beta-agonist is exceeded. Although the clinical significance of these effects is not known, caution is advised in the coadministration of beta-agonists with nonpotassium-sparing diuretics.

Digoxin

Mean decreases of 16% to 22% in serum digoxin levels were demonstrated after single-dose intravenous and oral administration of albuterol, respectively, to normal volunteers who had received digoxin for 10 days. The clinical significance of these findings for patients with obstructive airway disease who are receiving albuterol and digoxin on a chronic basis is unclear. Nevertheless, it would be prudent to carefully evaluate the serum digoxin levels in patients who are currently receiving digoxin and albuterol.

Carcinogenesis, Mutagenesis, Impairment of Fertility

In a 2-year study in Sprague-Dawley rats, albuterol sulfate caused a significant dose-related increase in the incidence of benign leiomyomas of the mesovarium at dietary doses of 2.0, 10, and 50 mg/kg (approximately 2, 8, and 40 times, respectively, the maximum recommended daily inhalation dose for adults on a mg/m^2 basis, or, approximately 3/5, 3, and 15 times, respectively, the maximum recommended daily inhalation dose in children on a mg/m^2 basis). In another study this effect was blocked by the coadministration of propranolol, a non-selective beta-adrenergic antagonist. In an 18-month study in CD-1 mice albuterol sulfate showed no evidence of tumorigenicity at dietary doses of up to 500 mg/kg (approximately 200 times the maximum recommended daily inhalation dose for adults on a mg/m^2 basis, or, approximately 75 times the maximum recommended daily inhalation dose for children on a mg/m^2 basis). In a 22-month study in the Golden hamster albuterol sulfate showed no evidence of tumorigenicity at dietary doses of up to 50 mg/kg (approximately 25 times the maximum recommended daily inhalation dose for adults on a mg/m^2 basis, or, approximately 10 times the maximum recommended daily inhalation dose for children on a mg/m^2basis). Albuterol sulfate was not mutagenic in the Ames test with or without metabolic activation using tester strains S. typhimurium TA1537, TA1538, and TA98 or E. coli WP2, WP2uvrA, and WP67. No forward mutation was seen in yeast strain S. cerevisiae S9 nor any mitotic gene conversion in yeast strain S. cerevisiae JD1 with or without metabolic activation. Fluctuation assays in S. typhimurium TA98 and E. coli WP2, both with metabolic activation, were negative. Albuterol sulfate was not clastogenic in a human peripheral lymphocyte assay or in an AH1 strain mouse micronucleus assay at intraperitoneal doses of up to 200 mg/kg.

Reproduction studies in rats demonstrated no evidence of impaired fertility at oral doses up to 50 mg/kg (approximately 40 times the maximum recommended daily inhalation dose for adults on a mg/m^2 basis).

Pregnancy

Teratogenic Effects: Pregnancy Category C: Albuterol has been shown to be teratogenic in mice. A study in CD-1 mice at subcutaneous (sc) doses of 0.025, 0.25, and 2.5 mg/kg (approximately 1/100, 1/10, and 1.0 times, respectively, the maximum recommended daily inhalation dose for adults on a mg/m^2 basis), showed cleft palate formation in 5 of 111 (4.5%) fetuses at 0.25 mg/kg and in 10 of 108 (9.3%) fetuses at 2.5 mg/kg. The drug did not induce cleft palate formation at the lowest dose, 0.025 mg/kg. Cleft palate also occurred in 22 of 72 (30.5%) fetuses from females treated with 2.5 mg/kg isoproterenol (positive control) subcutaneously, (approximately 1.0 times the maximum recommended daily inhalation dose for adults on a mg/m^2 basis).

A reproduction study in Stride Dutch rabbits revealed cranioschisis in 7 of 19 (37%) fetuses when albuterol was administered orally at a 50 mg/kg dose (approximately 80 times the maximum recommended daily inhalation dose for adults on a mg/m^2 basis).

There are no adequate and well-controlled studies in pregnant women. Albuterol should be used during pregnancy only if the potential benefit justifies the potential risk to the fetus.

During worldwide marketing experience, various congenital anomalies, including cleft palate and limb defects, have been rarely reported in the offspring of patients being treated with albuterol. Some of the mothers were taking multiple medications during their pregnancies. No consistent pattern of defects can be discerned, and a relationship between albuterol use and congenital anomalies has not been established.

Use in Labor and Delivery

Because of the potential for beta-agonist interference with uterine contractility, use of Albuterol Sulfate Inhalation Solution for relief of bronchospasm during labor should be restricted to those patients in whom the benefits clearly outweigh the risk.

Tocolysis

Albuterol has not been approved for the management of preterm labor. The benefit:risk ratio when albuterol is administered for tocolysis has not been established. Serious adverse reactions, including maternal pulmonary edema, have been reported during or following treatment of premature labor with beta2-agonists, including albuterol.

Nursing Mothers

It is not known whether this drug is excreted in human milk. Because of the potential for tumorigenicity shown for albuterol in some animal studies, a decision should be made whether to discontinue nursing or to discontinue the drug, taking into account the importance of the drug to the mother.

Pediatric Use

The safety and effectiveness of Albuterol Sulfate Inhalation Solution have been established in children 2 years of age or older. Use of Albuterol Sulfate Inhalation Solution in these age-groups is supported by evidence from adequate and well-controlled studies of Albuterol Sulfate Inhalation Solution in adults; the likelihood that the disease course, pathophysiology, and the drug's effect in pediatric and adult patients are substantially similar; and published reports of trials in pediatric patients 3 years of age or older. The recommended dose for the pediatric population is based upon three published dose comparison studies of efficacy and safety in children 5 to 17 years, and on the safety profile in both adults and pediatric patients at doses equal to or higher than the recommended doses. The safety and effectiveness of Albuterol Sulfate Inhalation Solution in children below 2 years of age have not been established.

ADVERSE REACTIONS

The results of clinical trials with Albuterol Sulfate Inhalation Solution, 0.5% in 135 patients showed the following side effects that were considered probably or possibly drug related:

Percent Incidence of Adverse Reactions

Reaction

Reaction Percent Incidence
n=135

Central Nervous System

Tremors 20%

Dizziness 7%

Nervousness 4%

Headache 3%

Sleeplessness 1%

Gastrointestinal

Nausea 4%

Dyspepsia 1%

Ear, nose, and throat

Nasal congestion 1%

Pharyngitis <1%

Cardiovascular

Tachycardia 1%

Hypertension 1%

Respiratory

Bronchospasm 8%

Cough 4%

Bronchitis 4%

Wheezing 1%

No clinically relevant laboratory abnormalities related to Albuterol Sulfate Inhalation Solution administration were determined in these studies.

Cases of urticaria, angioedema, rash, bronchospasm, hoarseness, oropharyngeal edema, and arrhythmias (including atrial fibrillation, supraventricular tachycardia, and extra-systoles) have also been reported after the use of inhaled albuterol.

OVERDOSAGE

The expected symptoms with overdosage are those of excessive betaadrenergic stimulation and/or occurrence or exaggeration of any of the symptoms listed under ADVERSE REACTIONS, e.g., seizures, angina, hypertension or hypotension, tachycardia with rates up to 200 beats per minute, arrhythmias, nervousness, headache, tremor, dry mouth, palpitation, nausea, dizziness, fatigue, malaise, and sleeplessness. Hypokalemia may also occur. In isolated cases in children 2 to 12 years of age, tachycardia with rates >200 beats/min has been observed.

As with all sympathomimetic medications, cardiac arrest and even death may be associated with abuse of Albuterol Sulfate Inhalation Solution. Treatment consists of discontinuation of Albuterol Sulfate Inhalation Solution together with appropriate symptomatic therapy. The judicious use of a cardioselective beta-receptor blocker may be considered, bearing in mind that such medication can produce bronchospasm. There is insufficient evidence to determine if dialysis is beneficial for overdosage of Albuterol Sulfate Inhalation Solution.

The oral median lethal dose of albuterol sulfate in mice is greater than 2000 mg/kg (approximately 810 times the maximum recommended daily inhalation dose for adults on a mg/m^2 basis, or, approximately 300 times the maximum recommended daily inhalation dose for children on a mg/m^2 basis). In mature rats, the subcutaneous (sc) median lethal dose of albuterol sulfate is approximately 450 mg/kg (approximately 365 times the maximum recommended daily inhalation dose for adults on a mg/m^2 basis, or, approximately 135 times the maximum recommended daily inhalation dose for children on a mg/m^2 basis). In small young rats, the sc median lethal dose is approximately 2000 mg/kg (approximately 1600 times the maximum recommended daily inhalation dose for adults on a mg/m^2 basis, or, approximately 600 times the maximum recommended daily inhalation dose for children on a mg/m^2 basis). The inhalational median lethal dose has not been determined in animals.

DOSAGE AND ADMINISTRATION

Adults and Children 2 to 12 Years of Age

The usual dosage for adults and for children weighing at least 15 kg is 2.5 mg of albuterol (one unit dose vial) administered three to four times daily by nebulization. Children weighing less than 15 kg who require less than 2.5 mg/dose (i.e., less than a full unit dose vial) should use Albuterol Sulfate Inhalation Solution, 0.5% instead of Albuterol Sulfate Inhalation Solution, 0.083%. More frequent administration or higher doses are not recommended. To administer 2.5 mg of albuterol, administer the entire contents of one sterile unit dose vial (3 mL of 0.083% inhalation solution) by nebulization. The flow rate is regulated to suit the particular nebulizer so that Albuterol Sulfate Inhalation Solution will be delivered over approximately 5 to 15 minutes.

The use of Albuterol Sulfate Inhalation Solution can be continued as medically indicated to control recurring bouts of bronchospasm. During this time most patients gain optimal benefit from regular use of the inhalation solution.

If a previously effective dosage regimen fails to provide the usual relief, medical advice should be sought immediately as this is often a sign of seriously worsening asthma that would require reassessment of therapy.

Drug compatibility (physical and chemical), efficacy, and safety of Albuterol Sulfate Inhalation Solution when mixed with other drugs in a nebulizer have not been established.

Microbial Contamination

To avoid microbial contamination, the entire contents of the unit-dose vial should be administered immediately after the vial has been opened for the first time. The nebulizer should be cleaned in accordance with the manufacturer's instructions. Failure to do so could lead to bacterial contamination of the nebulizer and possible infection.

HOW SUPPLIED

Albuterol Sulfate Inhalation Solution, 0.083% is contained in plastic sterile unit dose vials of 3 mL each, supplied in foil pouches:

NDC carton of 25 vials

NDC carton of 30 vials

NDC carton of 60 vials

Protect from light. Store between 2° and 25° C (36° and 77° F). Discard if solution becomes discolored. (Note: Albuterol Sulfate Inhalation Solution is a clear, colorless to light yellow solution.)

KEEP OUT OF REACH OF CHILDREN

Manufactured By:

Holopack International

Columbia, SC 29203

PATIENT'S INSTRUCTIONS FOR USE

Albuterol Sulfate

Inhalation Solution, 0.083%*

*Potency expressed as albuterol.

Read complete instructions carefully before using.

1. Twist open the top of one Albuterol Sulfate Inhalation Solution unit-of-use container and squeeze the entire contents into the nebulizer reservoir (Figure 1).

2. Connect the nebulizer reservoir to the mouthpiece or face mask (Figure 2).

3. Connect the nebulizer to the compressor.

4. Sit in a comfortable, upright position; place the mouthpiece in your mouth (Figure 3)(or put on the face mask); and turn on the compressor.

5. Breathe as calmly, deeply and evenly as possible until no more mist is formed in the nebulizer chamber (about 5 to 15 minutes). At this point, the treatment is finished.

6. Clean the nebulizer (see manufacturer's instructions). Failure to clean the nebulizer in accordance with the manufacturer's instructions could lead to bacterial contamination of the nebulizer and possible infection.

Note: Use only as directed by your doctor. More frequent administration or higher doses are not recommended.

The safety and effectiveness of Albuterol Sulfate Inhalation Solution have not been determined when one or more drugs are mixed with it in a nebulizer. Check with your doctor before mixing any medications in your nebulizer.

Microbial Contamination: To avoid microbial contamination, the entire contents of the unit-dose vial should be administered immediately after the vial has been opened for the first time.

Protect from light. Store between 2° and 25° C (36° and 77° F). Discard if solution becomes discolored. (Note: Albuterol Sulfate Inhalation Solution is a clear, colorless to light yellow solution.)

ADDITIONAL INSTRUCTIONS:

Manufactured By:

Holopack International

Columbia, SC 29203